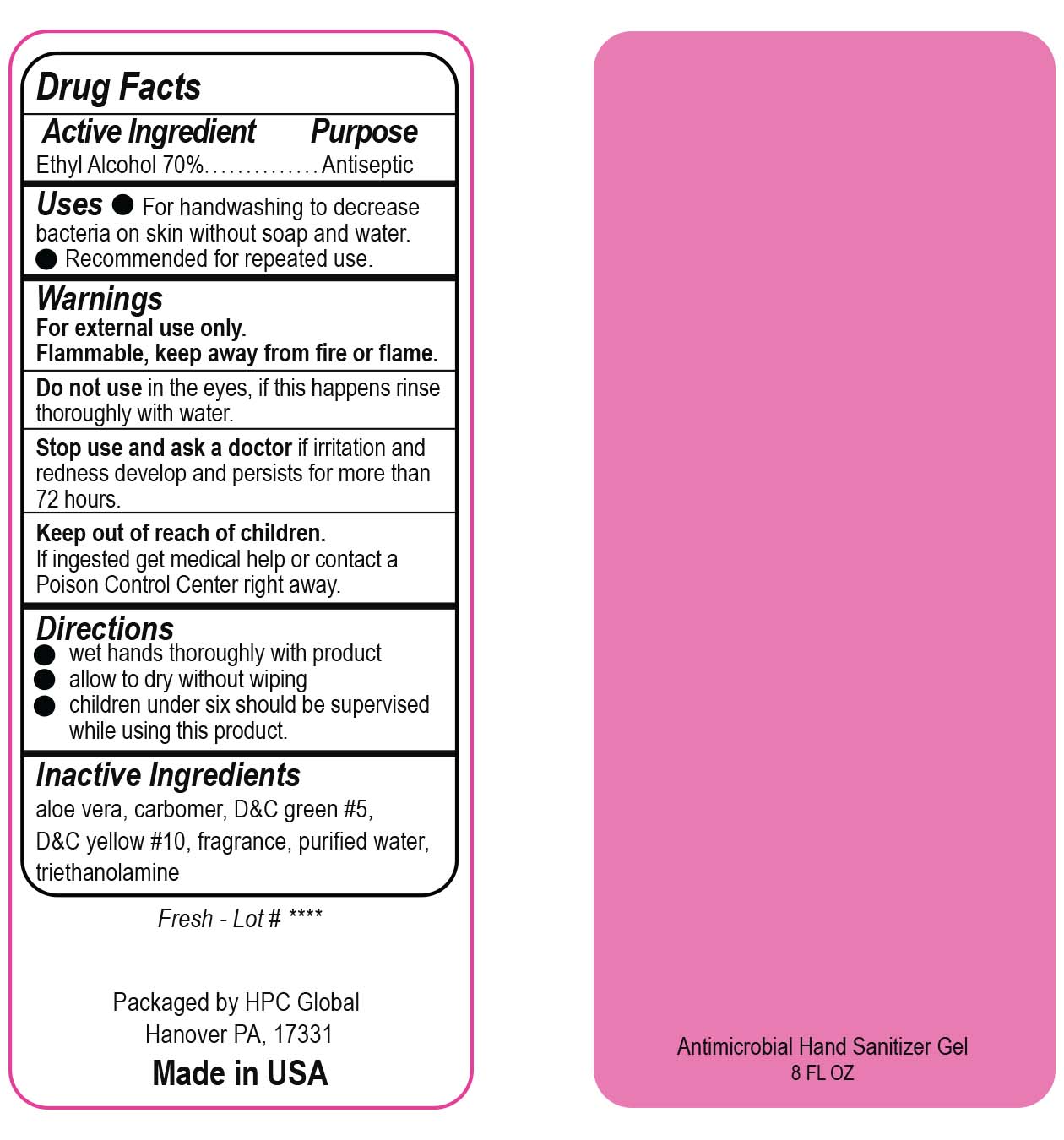 DRUG LABEL: Antimicrobial Hand Sanitizer
NDC: 51811-744 | Form: GEL
Manufacturer: Hanover Pen Corp dba HPC Global
Category: otc | Type: HUMAN OTC DRUG LABEL
Date: 20200720

ACTIVE INGREDIENTS: ALCOHOL 165.9 mL/237 mL
INACTIVE INGREDIENTS: TROLAMINE; CARBOMER INTERPOLYMER TYPE A (ALLYL SUCROSE CROSSLINKED); WATER; ALOE VERA LEAF; D&C GREEN NO. 5; D&C YELLOW NO. 10

(4744-601) Antimicrobial Hand Sanitizer 8 oz. Fresh Scent
alcohol gel

Active Indgredient

Ethyl Alcohol 70%

Purpose

Antiseptic

Uses

- For handwashing to decrease bacteria on skin.
- Recommended for repeated use.

Warnings

for external use only.

Flammable, keep away from fire or flame.

Do not use in the eyes, if this happens rinse thoroughly with water.

Stop use and ask a doctor if irritation and redness develop and persists for more than 72 hours.

Keep out of reach of children.

If ingested get medical help or contact a Poison Control Center right away.

Directions

- wet hands thoroughly with product allow to dry without wiping
- children under six should be supervised while using this product.

Inactive Ingredients

aloe vera, carbomer, D&C green #5, D&C yellow #10, fragrance, purified water, triethanolamine

Fresh - Lot# ****

Packaged by HPC Global

Hanover PA, 17331

Made in USA

PACKAGE LABEL

Antimicrobial Hand Sanitizer Gel

8 FL OZ

Drug Facts